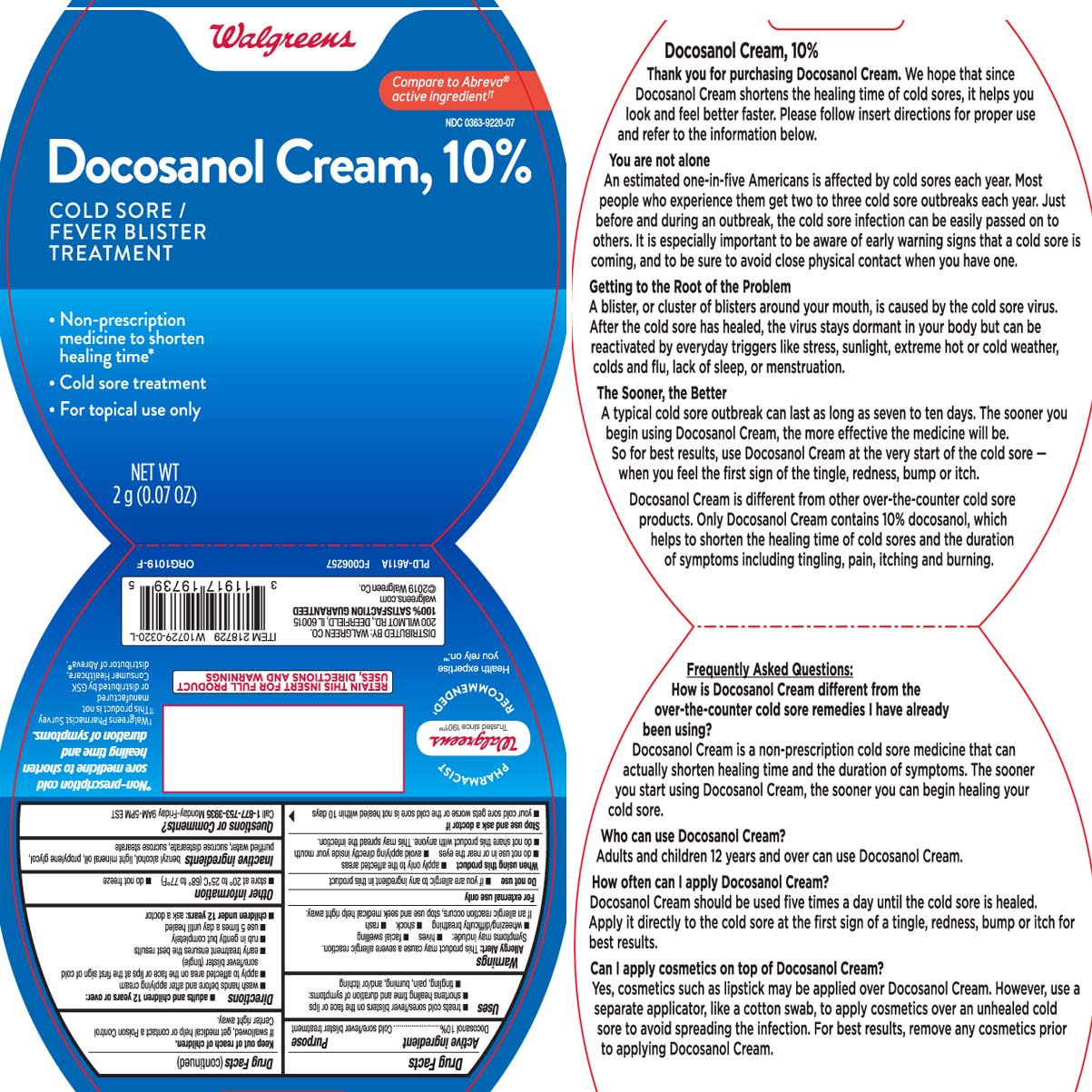 DRUG LABEL: Cold Sore Fever Blister Treatment
NDC: 0363-9220 | Form: CREAM
Manufacturer: Walgreens
Category: otc | Type: HUMAN OTC DRUG LABEL
Date: 20260115

ACTIVE INGREDIENTS: DOCOSANOL 100 mg/1 g
INACTIVE INGREDIENTS: BENZYL ALCOHOL; LIGHT MINERAL OIL; PROPYLENE GLYCOL; WATER; SUCROSE DISTEARATE (HLB 5); SUCROSE STEARATE

Docosanol Cream, 10%

Active ingredient

Docosanol 10%

Purpose

Cold sore/fever blister treatment

Uses

- treats cold sores/fever blisters on the face or lips
- shortens healing time and duration of symptoms:
- tingling, pain, burning, and/or itching

Warnings

Allergy Alert: This product may cause a severe allergic reaction. Symptoms may include:

- hives
- facial swelling
- wheezing/difficulty
- shock
- rash

If an allergic reaction occurs, stop use and seek medical help right away.

For external use only

Do not use

- if you are allergic to any ingredient in this product

When using this product

- apply only to the affected areas
- do not use in or near the eyes
- avoid applying directly inside your mouth
- do not share this product with anyone. This may spread the infection.

Stop use and ask a doctor if

- your cold sore gets worse or the cold sore is not healed within 10 days

Keep out of reach of children.

If swallowed, get medical help or contact a Poison Control Center right away.

Directions

- adults and children 12 years or over:
  - wash hands before and after applying cream
  - apply to affected area on the face or lips at the first sign of cold sore/fever blister (tingle).
  - early treatment ensures the best results
  - rub in gently but completely
  - use 5 times a day until healed
- children under 12 years: ask a doctor

Other information

- store at 20° to 25°C (68° to 77°F)
- do not freeze

Inactive ingredients

benzyl alcohol, light mineral oil, propylene glycol, purified water, sucrose distearate, sucrose stearate

Questions or comments?

Call 1-877-753-3935 Monday-Friday 9AM-5PM EST

Principal Display Panel

Compare to Abreva® active ingredient††

Docosanol Cream, 10%

COLD SORE / FEVER BLISTER TREATMENT

- Non-prescription medicine to shorten healing time*
- Cold sore treatment
- For Topical Use Only

NET WT 2 g (0.07 oz)

††This product is not manufactured or distributed by GSK Consumer Healthcare, distributor of Abreva®.

* Non-prescription cold sore medicine to shorten healing time and duration of symptpms.

RETAIN THIS INSERT FOR FULL PRODUCT USES, DIRECTIONS AND WARNINGS

DISTRIBUTED BY: WALGREEN CO.

200 WILMOT RD., DEERFIELD, IL 60015

walgreens.com

Package Label

WALGREENS Cold Sore Fever Blister Treatment